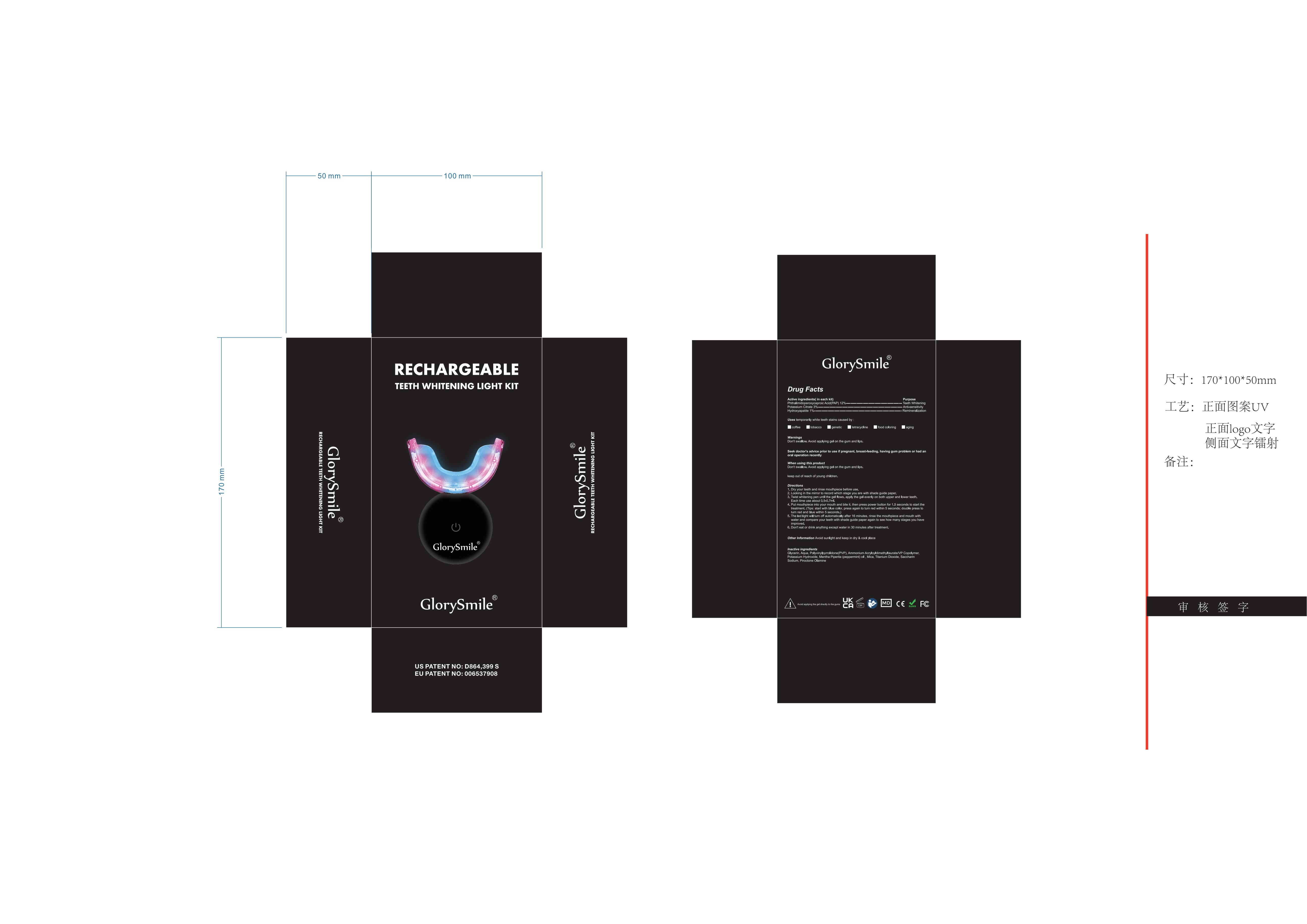 DRUG LABEL: TeethWhitening Kit
NDC: 83778-012 | Form: CREAM
Manufacturer: Jiangxi Dentalbright Technology Co., Ltd.
Category: otc | Type: HUMAN OTC DRUG LABEL
Date: 20241220

ACTIVE INGREDIENTS: POTASSIUM CITRATE 3 g/100 mL; PHTHALIMIDOPEROXYCAPROIC ACID 12 g/100 mL; TRIBASIC CALCIUM PHOSPHATE 1 g/100 mL
INACTIVE INGREDIENTS: AMMONIUM ACRYLOYLDIMETHYLTAURATE/VP COPOLYMER; PVP; GLYCERIN; PEPPERMINT OIL; SACCHARIN SODIUM; TITANIUM DIOXIDE; PIROCTONE OLAMINE; POTASSIUM HYDROXIDE; MICA; AQUA

ACTIVE INGREDIENT

Phthalimidoperoxycaproic Acid(PAP)
Potassium Citrate
Hydroxyapatite

PURPOSE

Teeth whitening, anti-sensitivity, remineralization

WHEN USING

Don't swallow. Avoidapplying gel on the gum and lips.

Stop treatment when feel severe pain

ASK DOCTOR

Stop treatment when feel severe pain

Keep out of reach of children.

DOSAGE AND ADMINISTRATION

1. Dry your teeth and rinse mouthpiece before use.
2. Looking in the mirror to record which stage you are with shade guide paper.
3. Twist whitening pen until the gel flows. apply the gel evenly on both upper and lower
teeth. Each time use about 0.5-0.7ml.
4. Put mouthpiece into your mouth and bite it, then press power button for 1.5 seconds
to start the treatment. (Tips: start with blue color, press again to turn red within 5
seconds; double press to turn red and blue within 5 seconds.)
5. The led light will turn off automatically after 16 minutes, rinse the mouthpiece and
mouth with water and compare your teeth with shade guide paper again to see how
many stages you have improved.
6. Don't eat or drink anything except water in 30 minutes after treatment.

INACTIVE INGREDIENT

Glycerin􀀀Aqua􀀀Polyvinylpyrrolidone(PVP)􀀀Ammonium
Acryloyldimethyltaurate/VP Copolymer􀀀Potassium Hydroxide􀀀Mentha Piperita
(peppermint) oil 􀀀Mica􀀀Titanium Dioxide􀀀Saccharin Sodium􀀀Piroctone Olamine
PRINCIPAL DISPLAY

WARNINGS

Don't swallow. Avoid applying gel on the gum and lips.Avoid sunlight and keep in dry & cool place

INDICATIONS AND USAGE

1. Dry your teeth and rinse mouthpiece before use

2. Looking in the mirror to recor which stage you are with shadeyuide paper.

3. Twist whitening pen until the gel flows. apply the gel evenly on bath upper and lower..teeth. Each time use about 0.5-0.7ml

4. Put mouthpiece into your mouth and bite it, then press power bltton for 1.5 secondst with blue color, press again to turn red within 5 to start the treatment.(Tips: stad and blue within 5 seconds.)seconds; double press to turn re

5. The led light will turn off automatically after 16 minutes, rinse themouthpiece andmouth with water and compareour teeth with shade guide paperagain to see howmany stages you have improved

6. Don't eat or drink anything exept water in 30 minutes after treatment.